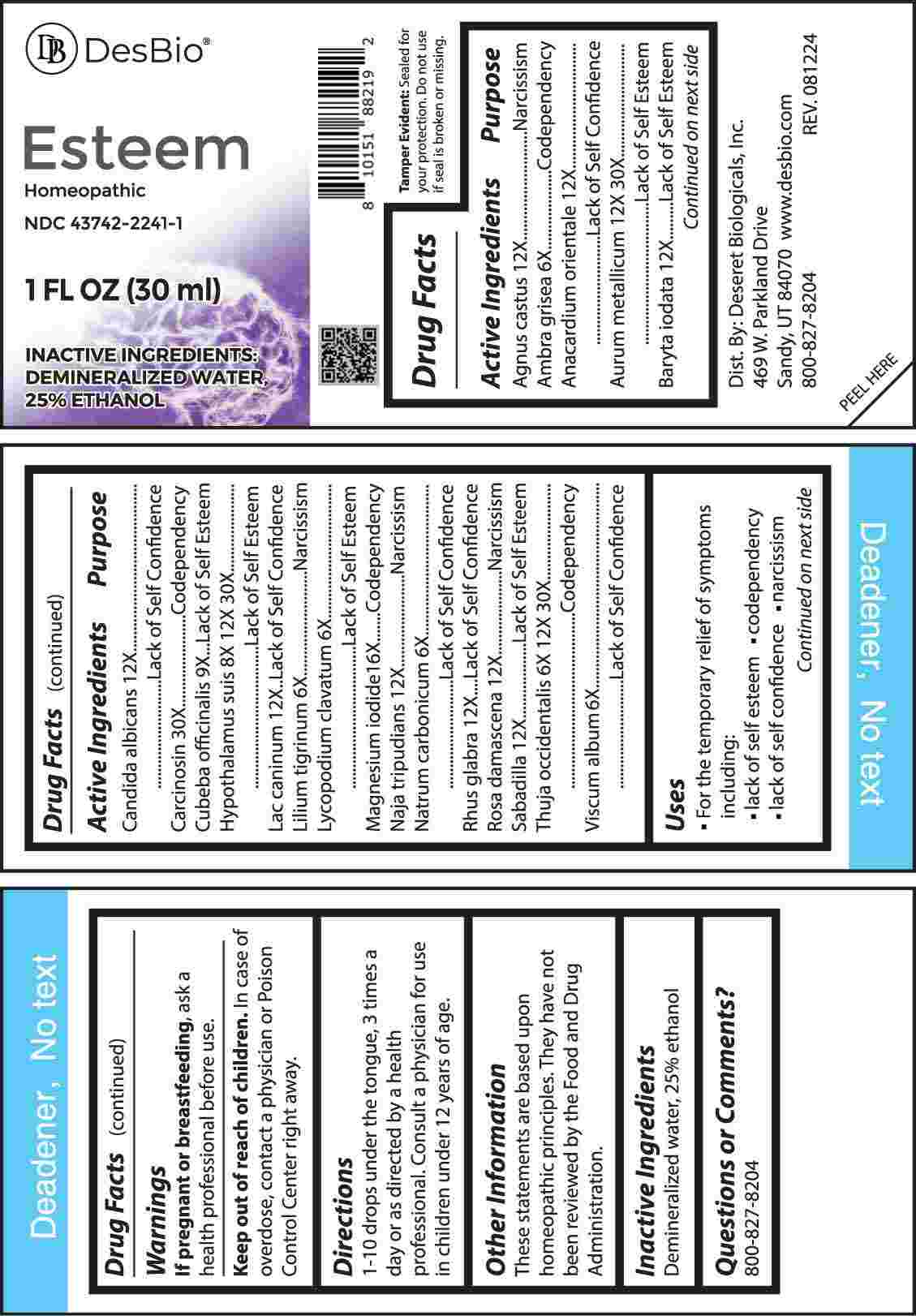 DRUG LABEL: Esteem
NDC: 43742-2241 | Form: LIQUID
Manufacturer: Deseret Biologicals, Inc.
Category: homeopathic | Type: HUMAN OTC DRUG LABEL
Date: 20241230

ACTIVE INGREDIENTS: CHASTE TREE FRUIT 12 [hp_X]/1 mL; AMBERGRIS 6 [hp_X]/1 mL; SEMECARPUS ANACARDIUM JUICE 12 [hp_X]/1 mL; GOLD 12 [hp_X]/1 mL; BARIUM IODIDE 12 [hp_X]/1 mL; CANDIDA ALBICANS 12 [hp_X]/1 mL; HUMAN BREAST TUMOR CELL 30 [hp_X]/1 mL; PIPER CUBEBA FRUIT 9 [hp_X]/1 mL; SUS SCROFA HYPOTHALAMUS 8 [hp_X]/1 mL; CANIS LUPUS FAMILIARIS MILK 12 [hp_X]/1 mL; LILIUM LANCIFOLIUM WHOLE FLOWERING 6 [hp_X]/1 mL; LYCOPODIUM CLAVATUM SPORE 6 [hp_X]/1 mL; MAGNESIUM IODIDE 16 [hp_X]/1 mL; NAJA NAJA VENOM 12 [hp_X]/1 mL; SODIUM CARBONATE 6 [hp_X]/1 mL; RHUS GLABRA TOP 12 [hp_X]/1 mL; ROSA X DAMASCENA FLOWERING TOP 12 [hp_X]/1 mL; SCHOENOCAULON OFFICINALE SEED 12 [hp_X]/1 mL; THUJA OCCIDENTALIS LEAFY TWIG 6 [hp_X]/1 mL; VISCUM ALBUM FRUITING TOP 6 [hp_X]/1 mL
INACTIVE INGREDIENTS: WATER; ALCOHOL

DRUG FACTS:

ACTIVE INGREDIENTS:

Agnus Castus 12X, Ambra Grisea 6X, Anacardium Orientale 12X, Aurum Metallicum 12X, 30X, Baryta Iodata 12X, Candida Albicans 12X, Carcinosin 30X, Cubeba Officinalis 9X, Hypothalamus Suis 8X, 12X, 30X, Lac Caninum 12X, Lilium Tigrinum 6X, Lycopodium Clavatum 6X, Magnesium Iodide 16X, Naja Tripudians 12X, Natrum Carbonicum 6X, Rhus Glabra 12X, Rosa Damascena 12X, Sabadilla 12X, Thuja Occidentalis 6X, 12X, 30X, Viscum Album 6X.

PURPOSE:

Agnus Castus - Narcissism, Ambra Grisea - Codependency, Anacardium Orientale – Lack of Self Confidence, Aurum Metallicum – Lack of Self Esteem, Baryta Iodata – Lack of Self Esteem, Candida Albicans – Lack of Confidence, Carcinosin - Codependency, Cubeba Officinalis – Lack of Self Esteem, Hypothalamus Suis – Lack of Self Esteem, Lac Caninum – Lack of Self Confidence, Lilium Tigrinum - Narcissism, Lycopodium Clavatum – Lack of Self Esteem , Magnesium Iodide - Codependency, Naja Tripudians - Narcissism, Natrum Carbonicum – Lack of Self Confidence, Rhus Glabra – Lack of Self Confidence, Rosa Damascena - Narcissism, Sabadilla – Lack of Self Esteem, Thuja Occidentalis - Codependency, Viscum Album – Lack of Self Confidence.

USES:

• For the temporary relief of the symptoms including:

• lack of self esteem • codependency • lack of self confidence • narcissism

These statements are based upon homeopathic principles. They have not been reviewed by the Food and Drug Administration.

WARNINGS:

If pregnant or breastfeeding, ask a health professional before use.

Keep out of reach of children. In case of overdose, contact a physician or Poison Control Center right away.

Tamper Evident: Sealed for your protection. Do not use if seal is broken or missing.

KEEP OUT OF REACH OF CHILDREN:

In case of overdose, contact a physician or Poison Control Center right away.

DIRECTIONS:

1-10 drops under the tongue, 3 times a day or as directed by a health professional. Consult a physician for use in children under 12 years of age.

INACTIVE INGREDIENTS:

Demineralized water, 25% ethanol

QUESTIONS:

Dist. By: Deseret Biologicals, Inc.

469 W. Parkland Drive

Sandy, UT 84070

www.desbio.com

800-827-8204

PACKAGE LABEL DISPLAY:

DesBio

Esteem

Homeopathic
NDC 43742-2241-1
1 FL OZ (30 ml)